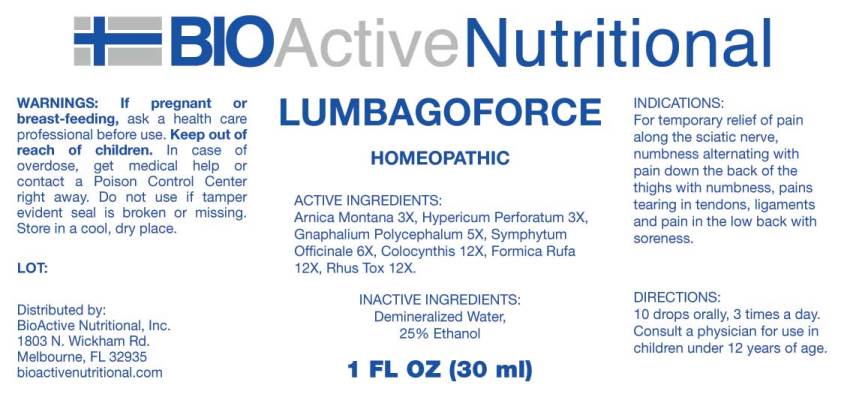 DRUG LABEL: Lumbagoforce
NDC: 43857-0434 | Form: LIQUID
Manufacturer: BioActive Nutritional, Inc.
Category: homeopathic | Type: HUMAN OTC DRUG LABEL
Date: 20170301

ACTIVE INGREDIENTS: ARNICA MONTANA 3 [hp_X]/1 mL; HYPERICUM PERFORATUM 3 [hp_X]/1 mL; PSEUDOGNAPHALIUM OBTUSIFOLIUM 5 [hp_X]/1 mL; COMFREY ROOT 6 [hp_X]/1 mL; CITRULLUS COLOCYNTHIS FRUIT PULP 12 [hp_X]/1 mL; FORMICA RUFA 12 [hp_X]/1 mL; TOXICODENDRON PUBESCENS LEAF 12 [hp_X]/1 mL
INACTIVE INGREDIENTS: WATER; ALCOHOL

Drug Facts:

ACTIVE INGREDIENTS:

Arnica Montana 3X, Hypericum Perforatum 3X, Gnaphalium Polycephalum 5X, Symphytum Officinale 6X, Colocynthis 12X, Formica Rufa 12X, Rhus Tox 12X.

INDICATIONS:

For temporary relief of pain along the sciatic nerve, numbness alternating with pain down the back of the thighs with numbness, pains tearing in tendons, ligaments and pain in the low back with soreness.

WARNING:

If pregnant or breast-feeding, ask a health care professional before use.

Keep out of reach of children. In case of overdose, get medical help or contact a Poison Control Center right away.

Do not use if tamper evident seal is broken or missing.

Store in cool, dry place.

Keep out of reach of children. In case of overdose, get medical help or contact a Poison Control Center right away.

DIRECTIONS:

10 drops orally, 3 times a day. Consult a physician for use in children under 12 years of age.

INDICATIONS:

For temporary relief of pain along the sciatic nerve, numbness alternating with pain down the back of the thighs with numbness, pains tearing in tendons, ligaments and pain in the low back with soreness.

INACTIVE INGREDIENTS:

Demineralized Water, 25% Ethanol.

QUESTIONS:

Distributed by:

BioActive Nutritional, Inc.

1803 N. Wickham Rd.

Melbourne, FL 32935

bioactivenutritional.com

PACKAGE LABEL DISPLAY:

BIOActive Nutritional

LUMBAGOFORCE

HOMEOPATHIC

1 FL OZ (30 ml)